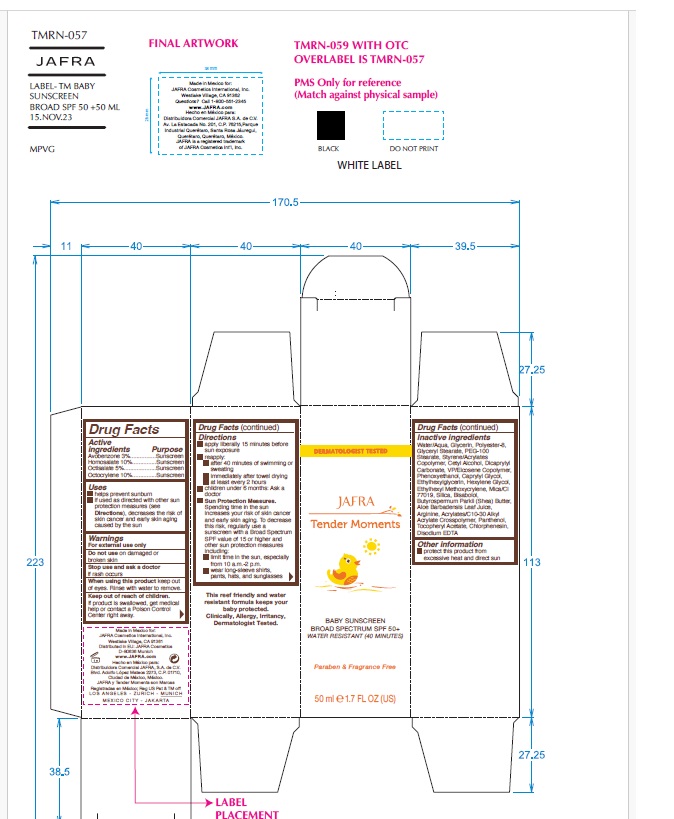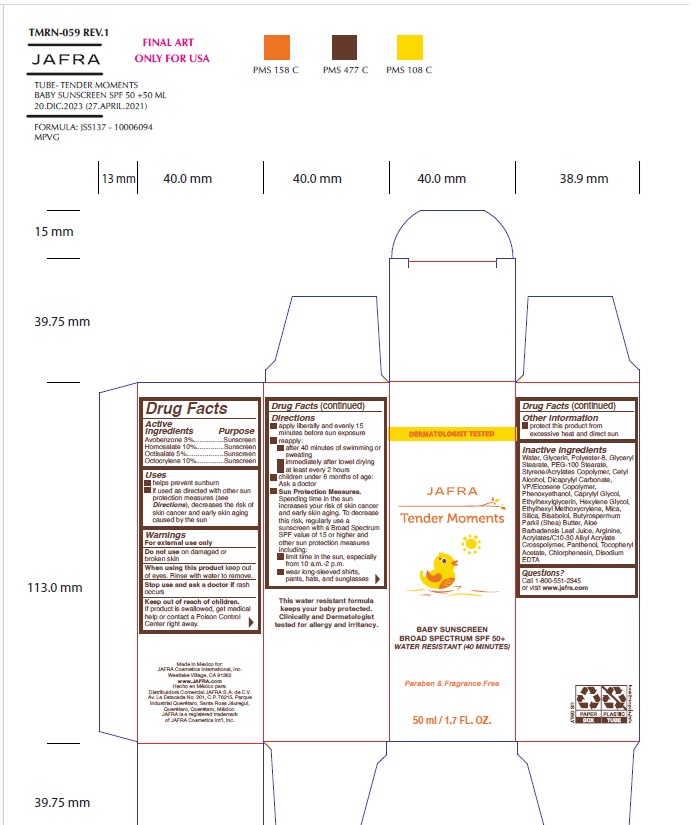 DRUG LABEL: Tender Moments Baby Sunscreen Broad Spectrum SPF 50 Water Resistant (40 minutes)
NDC: 68828-444 | Form: CREAM
Manufacturer: Distribuidora Comercial Jafra, S.A. de C.V.
Category: otc | Type: HUMAN OTC DRUG LABEL
Date: 20250102

ACTIVE INGREDIENTS: AVOBENZONE 3 g/100 mL; HOMOSALATE 10 g/100 mL; OCTISALATE 5 g/100 mL; OCTOCRYLENE 10 g/100 mL
INACTIVE INGREDIENTS: POLYESTER-8 (1400 MW, CYANODIPHENYLPROPENOYL CAPPED); VINYLPYRROLIDONE/EICOSENE COPOLYMER; HEXYLENE GLYCOL; MICA; PHENOXYETHANOL; CAPRYLYL GLYCOL; WATER; CETYL ALCOHOL; DICAPRYLYL CARBONATE; ETHYLHEXYL METHOXYCRYLENE; ETHYLHEXYLGLYCERIN; SILICON DIOXIDE; LEVOMENOL; SHEA BUTTER; ALOE VERA LEAF; CARBOMER COPOLYMER TYPE B (ALLYL PENTAERYTHRITOL CROSSLINKED); PANTHENOL; .ALPHA.-TOCOPHEROL ACETATE; CHLORPHENESIN; EDETATE DISODIUM; ARGININE; GLYCERYL MONOSTEARATE; PEG-100 STEARATE; GLYCERIN

Tender Moments Baby Sunscreen Broad Spectrum SPF 50+ Water Resistant (40 minutes)

Active ingredients Purpose

Avobenzone 3% Sunscreen

Homosalate 10% Sunscreen

Octisalate 5% Sunscreen

Octocrylene 10% Sunscreen

Uses

- Helps Prevent Sunburn
- If used as directed with other sun protection measures (see Directions), decreases the risk of skin cancer and early skin aging caused by the sun.

Warnings

For external use only

Do not use on damaged or broken skin

When using this product keep out of eyes. Rinse with water to remove

Stop use and ask a doctor ifrash occurs.

Keep out of reach of children. If product is swallowed, get medical help or contact a poison Control Center right away

Directions

- apply liberally and evenly 15 minutes before sun exposure
- reapply:

• after 40 minutes of swimming or sweating

• immediately after towel drying

• at least every 2 hours

- children under 6 months of age : Ask a doctor

Sun Protection Measures Spending time in the sun increases your risk of skin cancer and early skin aging. To decrease this risk, regularly use a sunscreen with a Broad Spectrum SPF value of 15 or higher and other sun
protection measures including:

- limit time in the sun, especially from 10 a.m. – 2 p.m.
- wear long-sleeved shirts, pants, hats, and sunglasses

Other information

- protect this product from excessive heat and direct sun

Inactive ingredients

Water, Glycerin, Polyester-8, Glyceryl Stearate, PEG-100 Stearate, Styrene/Acrylates Copolymer, Cetyl Alcohol, Dicaprylyl Carbonate, VP/Eicosene Copolymer, Phenoxyethanol, Caprylyl Glycol, Ethylhexylglycerin, Hexylene Glycol, Ethylhexyl Methoxycrylene, Mica, Silica, Bisabolol, Butyrospermum Parkii (Shea) Butter, Aloe Barbadensis Leaf Juice, Arginine, Acrylates/C10-30 Alkyl Acrylate Crosspolymer, Panthenol, Tocopheryl Acetate, Chlorphenesin, Disodium EDTA

Questions?Call 1-800-551-2345 or visit www.jafra.com